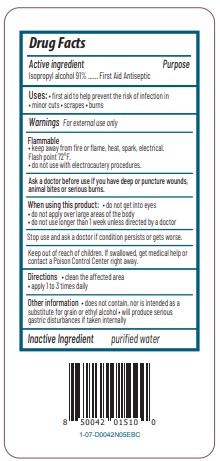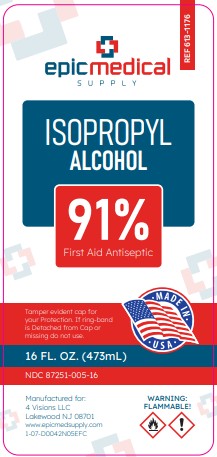 DRUG LABEL: Isopropyl Alcohol
NDC: 87251-005 | Form: LIQUID
Manufacturer: 4 Visions LLC
Category: otc | Type: HUMAN OTC DRUG LABEL
Date: 20260223

ACTIVE INGREDIENTS: ISOPROPYL ALCOHOL 91 mL/100 mL
INACTIVE INGREDIENTS: WATER

Epic Medical Isopropyl Alcohol 91%

Drug Facts

Active ingredient

Isopropyl alcohol 91%

Purpose

First Aid Antiseptic

Uses

- first aid to help prevent the risk of infection in:
  - minor cuts
  - scrapes
  - burns

Warnings

For external use only

Flammable

- keep away from fire or flame, heat, spark, electrical. Flash point 72°F.

Ask a doctor before use if you havedeep or puncture wounds, animal bites or serious burns

When using this product

- do not get into eyes
- do not apply over large areas of the body
- do not use longer than 1 week unless directed by a doctor

Stop use and ask a doctor ifcondition persists or gets worse

Keep out of reach of children.If swallowed, get medical help or contact a Poison Control Center right away.

Directions

- clean the affected area
- apply 1 to 3 times daily

Other information

- does not contain, nor is intended as a substitute for grain or ethyl alcohol
- will produce serious gastric disturbances if taken internally

Inactive ingredient

purified water

PRINCIPAL DISPLAY PANEL

Epic Medical Supply

91% by Volume

ISOPROPYL ALCOHOL

First Aid Antiseptic

Square bottle uses less plastic than a similarly sized round bottle

Recyclable (If available in your area)

TAMPER EVIDENT CAP FOR YOUR PROTECTION.

IF RING-BAND IS DETACHED FROM CAP OR MISSING DO NOT USE.

Warning

Flammable

Manufactured for

4 Visions LLC

Lakewood New Jersey 08701

www.epicmedsupply.com

16 FL. OZ. (473 mL)